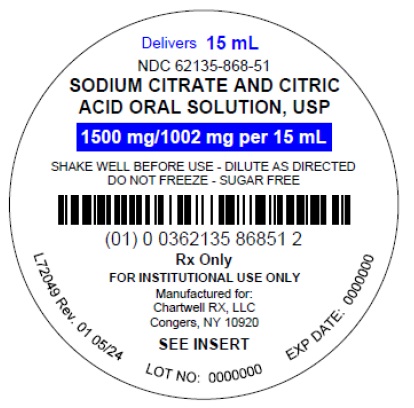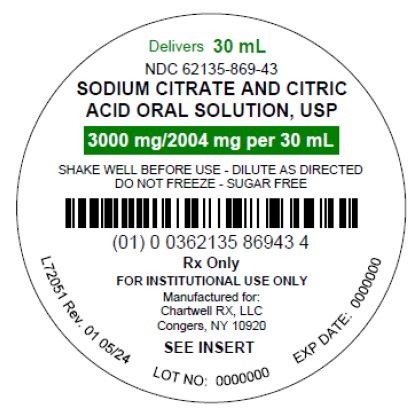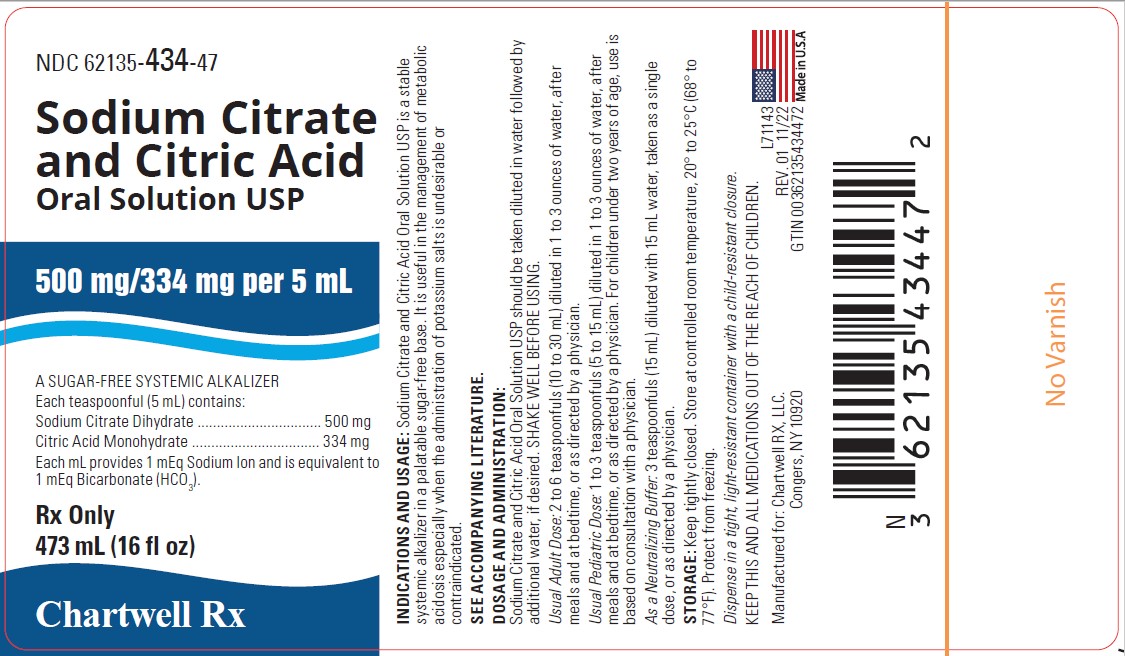 DRUG LABEL: Sodium Citrate and Citric Acid
NDC: 62135-434 | Form: SOLUTION
Manufacturer: Chartwell RX, LLC
Category: prescription | Type: HUMAN PRESCRIPTION DRUG LABEL
Date: 20240531

ACTIVE INGREDIENTS: SODIUM CITRATE 500 mg/5 mL; CITRIC ACID MONOHYDRATE 334 mg/5 mL
INACTIVE INGREDIENTS: SACCHARIN SODIUM; SODIUM BENZOATE; SORBITOL SOLUTION; WATER

Sodium Citrate and Citric Acid Oral Solution, USP

A Sugar-Free Systemic Alkalizer

DESCRIPTION

Sodium Citrate and Citric Acid Oral Solution, USP is a clear stable and cherry flavored systemic alkalizer containing sodium citrate and citric acid in a sugar-free base with cherry flavor. It is a nonparticulate neutralizing buffer.

Sodium Citrate and Citric Acid Oral Solution, USP contains in each teaspoonful (5 mL):

Sodium Citrate Dihydrate, USP 500 mg (0.34 Molar)
Citric Acid Monohydrate, USP 334 mg (0.32 Molar)

Each mL contains 1 mEq sodium ion and is equivalent to 1 mEq bicarbonate (HCO3).

INACTIVE INGREDIENTS: purified water, saccharin sodium, sodium benzoate, sorbitol solution, and wild cherry flavor.

CLINICAL PHARMACOLOGY

Sodium citrate is absorbed and metabolized to sodium bicarbonate, thus acting as a systemic alkalizer. The effects are essentially those of chlorides before absorption and those of bicarbonates subsequently. Oxidation is virtually complete so that less than 5% of sodium citrate is excreted in the urine unchanged.

INDICATIONS AND USAGE

Sodium citrate and citric acid oral solution, is an effective alkalinizing agent. It is useful in those conditions where long-term maintenance of an alkaline urine is desirable, and is of value in the alleviation of chronic metabolic acidosis, such as results from chronic renal insufficiency or the syndrome of renal tubular acidosis, especially when the administration of potassium salts is undesirable or contraindicated. This product is also useful for buffering and neutralizing gastric hydrochloric acid quickly and effectively.

Sodium citrate and citric acid oral solution is concentrated, and when administered after meals and before bedtime, allows one to maintain an alkaline urinary pH around the clock, usually without the necessity of a 2 A.M. dose. This product alkalinizes the urine without producing a systemic alkalosis in the recommended dosage. This product is highly palatable, pleasant tasting, and tolerable, even when administered for long periods.

CONTRAINDICATIONS

Patients on sodium-restricted diets or with severe renal impairment.

PRECAUTIONS

Sodium citrate and citric acid oral solution should be used with caution by patients with low urinary output unless under the supervision of a physician. This product should not be administered concurrently with aluminum-based antacids. Patients should be directed to dilute adequately with water and preferably, to take each dose after meals to avoid saline laxative effect. Sodium salts should be used cautiously in patients with cardiac failure, hypertension, impaired renal function, peripheral and pulmonary edema, and toxemia of pregnancy. Periodic examinations and determinations of serum electrolytes, particularly serum bicarbonate level, should be carried out in those patients with renal disease in order to avoid these complications.

ADVERSE REACTIONS

Sodium citrate and citric acid oral solution is generally well tolerated, without any unpleasant side effects, when given in recommended doses to patients with normal renal function and urinary output. However, as with any alkalinizing agent, caution must be used in certain patients with abnormal renal mechanisms to avoid development of alkalosis, especially in the presence of hypocalcemia.

OVERDOSAGE

Overdosage with sodium salts may cause diarrhea, nausea and vomiting, hypernoia, and convulsions.

DOSAGE AND ADMINISTRATION

Sodium citrate and citric acid oral solution should be taken diluted in water, followed by additional water, if desired. SHAKE WELL BEFORE USING.

For Systemic Alkalization

Usual Adult Dose

2 to 6 teaspoonfuls (10 to 30 mL), diluted in 1 to 3 ounces of water, after meals and at bedtime, or as directed by a physician.

Usual Pediatric Dose

1 to 3 teaspoonfuls (5 to 15 mL), diluted in 1 to 3 ounces of water, after meals and at bedtime, or as directed by a physician. For children under two years of age, use is based on consultation with a physician.

As a neutralizing buffer

3 teaspoonfuls (15 mL), diluted with 15 mL water, taken as a single dose, or as directed by a physician.

HOW SUPPLIED

Sodium Citrate and Citric Acid Oral Solution, USP (Colorless liquid with cherry flavor) is supplied in the following oral dosage form:

473 mL (16 fl oz) bottle : NDC 62135-434-47
Unit Dose Cup 15 mL : NDC 62135-868-51
20 Unit Dose Cups of 15 mL each : NDC 62135-868-24
Unit Dose Cup 30 mL : NDC 62135-869-43
20 Unit Dose Cups of 30 mL each : NDC 62135-869-24

STORAGE:

Keep tightly closed. Store at controlled room temperature, 20°-25°C (68°-77°F). Protect from freezing.

Rx ONLY

Manufactured for:
Chartwell RX, LLC
Congers, NY 10920

L71144

Rev. 03/2024

PACKAGE LABEL-PRINCIPAL DISPLAY PANEL

Sodium Citrate and Citric Acid Oral Solution, USP 500 mg/334 mg per 5 mL - NDC 62135-434-47 - 473 mL Bottle Label

Sodium Citrate and Citric Acid Oral Solution, USP 1500 mg/1002 mg per 15 mL - NDC 62135-868-51 - 15 mL Unit Dose Label

Sodium Citrate and Citric Acid Oral Solution, USP 3000 mg/2004 mg per 30 mL - NDC 62135-869-43 - 30 mL Unit Dose Label